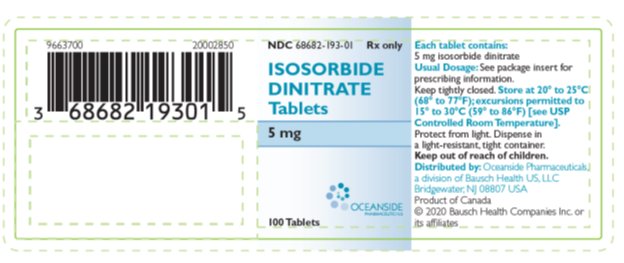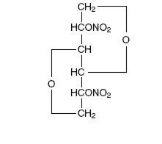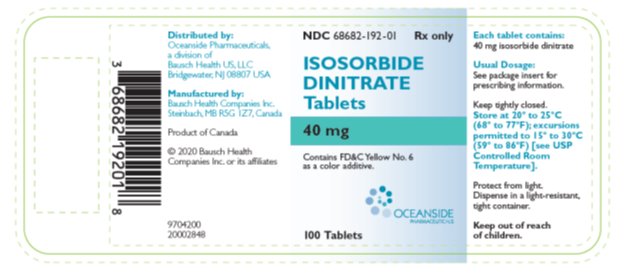 DRUG LABEL: Isosorbide Dinitrate
NDC: 68682-193 | Form: TABLET
Manufacturer: Oceanside Pharmaceuticals
Category: prescription | Type: HUMAN PRESCRIPTION DRUG LABEL
Date: 20200302

ACTIVE INGREDIENTS: ISOSORBIDE DINITRATE 5 mg/1 1
INACTIVE INGREDIENTS: MAGNESIUM STEARATE; FD&C RED NO. 40; LACTOSE MONOHYDRATE; MICROCRYSTALLINE CELLULOSE

Isosorbide Dinitrate
Tablets

DESCRIPTION

Isosorbide dinitrate (ISDN) is 1,4:3,6-dianhydro-D-glucitol 2,5-dinitrate, an organic nitrate whose structural formula is

and whose molecular weight is 236.14. The organic nitrates are vasodilators, active on both arteries and veins.

Isosorbide dinitrate is a white, crystalline, odorless compound which is stable in air and in solution, has a melting point of 70°C and has an optical rotation of +134° (c=1.0, alcohol, 20°C). Isosorbide dinitrate is freely soluble in organic solvents such as acetone, alcohol, and ether, but is only sparingly soluble in water.

Each Isosorbide Dinitrate tablet contains 5 mg or 40 mg of isosorbide dinitrate. The inactive ingredients in 5 mg tablet are magnesium stearate, lactose monohydrate, microcrystalline cellulose and FD&C red 40. The inactive ingredients in 40 mg tablet are magnesium stearate, microcrystalline cellulose, FD&C yellow 6, D&C yellow 10, and FD&C blue.

CLINICAL PHARMACOLOGY

The principal pharmacological action of isosorbide dinitrate is relaxation of vascular smooth muscle and consequent dilatation of peripheral arteries and veins, especially the latter. Dilatation of the veins promotes peripheral pooling of blood and decreases venous return to the heart, thereby reducing left ventricular end-diastolic pressure and pulmonary capillary wedge pressure (preload). Arteriolar relaxation reduces systemic vascular resistance, systolic arterial pressure, and mean arterial pressure (afterload). Dilatation of the coronary arteries also occurs. The relative importance of preload reduction, afterload reduction, and coronary dilatation remains undefined.

Dosing regimens for most chronically used drugs are designed to provide plasma concentrations that are continuously greater than a minimally effective concentration. This strategy is inappropriate for organic nitrates. Several well-controlled clinical trials have used exercise testing to assess the anti-anginal efficacy of continuously delivered nitrates. In the large majority of these trials, active agents were no more effective than placebo after 24 hours (or less) of continuous therapy. Attempts to overcome nitrate tolerance by dose escalation, even to doses far in excess of those used acutely, have consistently failed. Only after nitrates have been absent from the body for several hours has their anti-anginal efficacy been restored.

Pharmacokinetics

Absorption of isosorbide dinitrate after oral dosing is nearly complete, but bioavailability is highly variable (10% to 90%), with extensive first-pass metabolism in the liver. Serum levels reach their maxima about an hour after ingestion. The average bioavailability of ISDN is about 25%; most studies have observed progressive increases in bioavailability during chronic therapy.

Once absorbed, the volume of distribution of isosorbide dinitrate is 2 to 4 L/kg, and this volume is cleared at the rate of 2 to 4 L/min, so ISDN's half-life in serum is about an hour. Since the clearance exceeds hepatic blood flow, considerable extra hepatic metabolism must also occur. Clearance is affected primarily by denitration to the 2-mononitrate (15% to 25%) and the 5-mononitrate (75% to 85%).

Both metabolites have biological activity, especially the 5-mononitrate. With an overall half-life of about 5 hours, the 5-mononitrate is cleared from the serum by denitration to isosorbide, glucuronidation to the 5-mononitrate glucuronide, and denitration/hydration to sorbitol. The 2-mononitrate has been less well studied, but it appears to participate in the same metabolic pathways, with a half-life of about 2 hours.

The daily dose-free interval sufficient to avoid tolerance to organic nitrates has not been well defined. Studies of nitroglycerin (an organic nitrate with a very short half-life) have shown that daily dose-free intervals of 10 to 12 hours are usually sufficient to minimize tolerance. Daily dose-free intervals that have succeeded in avoiding tolerance during trials of moderate doses (e.g., 30 mg) of immediate-release ISDN have generally been somewhat longer (at least 14 hours), but this is consistent with the longer half-lives of ISDN and its active metabolites.

Few well-controlled clinical trials of organic nitrates have been designed to detect rebound or withdrawal effects. In one such trial, however, subjects receiving nitroglycerin had less exercise tolerance at the end of the daily dose-free interval than the parallel group receiving placebo. The incidence, magnitude, and clinical significance of similar phenomena in patients receiving ISDN have not been studied.

Clinical Trials

In clinical trials, immediate-release oral isosorbide dinitrate has been administered in a variety of regimens, with total daily doses ranging from 30 mg to 480 mg. Controlled trials of single oral doses of isosorbide dinitrate have demonstrated effective reductions in exercise-related angina for up to 8 hours. Anti-anginal activity is present about 1 hour after dosing.

Most controlled trials of multiple-dose oral ISDN taken every 12 hours (or more frequently) for several weeks have shown statistically significant anti-anginal efficacy for only 2 hours after dosing. Once-daily regimens, and regimens with one daily dose-free interval of at least 14 hours (e.g., a regimen providing doses at 8 am, 2 pm, and 6 pm), have shown efficacy after the first dose of each day that was similar to that shown in the single-dose studies cited above. The effects of the second and later doses have been smaller and shorter-lasting than the effect of the first.

From large, well-controlled studies of other nitrates, it is reasonable to believe that the maximal achievable daily duration of anti-anginal effect from isosorbide dinitrate is about 12 hours. No dosing regimen for isosorbide dinitrate, however, has ever actually been shown to achieve this duration of effect. One study of 8 patients, who were administered a pretitrated dose (average 27.5 mg) of immediate-release ISDN at 8 am, 1 pm, and 6 pm for 2 weeks, revealed that significant anti-anginal effectiveness was discontinuous and totaled about 6 hours in a 24-hour period.

INDICATIONS AND USAGE

Isosorbide Dinitrate tablets are indicated for the prevention of angina pectoris due to coronary artery disease. The onset of action of immediate-release oral isosorbide dinitrate is not sufficiently rapid for this product to be useful in aborting an acute anginal episode.

CONTRAINDICATIONS

Isosorbide Dinitrate is contraindicated in patients who are allergic to isosorbide dinitrate or any of its ingredients.

Do not use Isosorbide Dinitrate in patients who are taking certain drugs for erectile dysfunction (phosphodiesterase inhibitors), such as sildenafil, tadalafil, or vardenafil. Concomitant use can cause severe hypotension, syncope, or myocardial ischemia.

Do not use Isosorbide Dinitrate in patients who are taking the soluble guanylate cyclase stimulator riociguat. Concomitant use can cause hypotension.

WARNINGS

Amplification of the vasodilatory effects of Isosorbide Dinitrate by sildenafil can result in severe hypotension. The time course and dose dependence of this interaction have not been studied. Appropriate supportive care has not been studied, but it seems reasonable to treat this as a nitrate overdose, with elevation of the extremities and with central volume expansion.

The benefits of immediate-release oral isosorbide dinitrate in patients with acute myocardial infarction or congestive heart failure have not been established. If one elects to use isosorbide dinitrate in these conditions, careful clinical or hemodynamic monitoring must be used to avoid the hazards of hypotension and tachycardia. Because the effects of oral isosorbide dinitrate are so difficult to terminate rapidly, this formulation is not recommended in these settings.

PRECAUTIONS

General

Severe hypotension, particularly with upright posture, may occur with even small doses of isosorbide dinitrate. This drug should therefore be used with caution in patients who may be volume depleted or who, for whatever reason, are already hypotensive. Hypotension induced by isosorbide dinitrate may be accompanied by paradoxical bradycardia and increased angina pectoris.

Nitrate therapy may aggravate the angina caused by hypertrophic cardiomyopathy.

As tolerance to isosorbide dinitrate develops, the effect of sublingual nitroglycerin on exercise tolerance, although still observable, is somewhat blunted.

Some clinical trials in angina patients have provided nitroglycerin for about 12 continuous hours of every 24-hour day. During the daily dose-free interval in some of these trials, anginal attacks have been more easily provoked than before treatment, and patients have demonstrated hemodynamic rebound and decreased exercise tolerance. The importance of these observations to the routine, clinical use of immediate-release oral isosorbide dinitrate is not known.

In industrial workers who have had long-term exposure to unknown (presumably high) doses of organic nitrates, tolerance clearly occurs. Chest pain, acute myocardial infarction, and even sudden death have occurred during temporary withdrawal of nitrates from these workers, demonstrating the existence of true physical dependence.

Information for Patients

Patients should be told that the anti-anginal efficacy of isosorbide dinitrate is strongly related to its dosing regimen, so the prescribed schedule of dosing should be followed carefully. In particular, daily headaches sometimes accompany treatment with isosorbide dinitrate. In patients who get these headaches, the headaches are a marker of the activity of the drug. Patients should resist the temptation to avoid headaches by altering the schedule of their treatment with isosorbide dinitrate, since loss of headache may be associated with simultaneous loss of anti-anginal efficacy. Aspirin and/or acetaminophen, on the other hand, often successfully relieve isosorbide dinitrate-induced headaches with no deleterious effect on isosorbide dinitrate's anti-anginal efficacy.

Treatment with isosorbide dinitrate may be associated with lightheadedness on standing, especially just after rising from a recumbent or seated position. This effect may be more frequent in patients who have also consumed alcohol.

Drug Interactions

The vasodilating effects of isosorbide dinitrate may be additive with those of other vasodilators. Alcohol, in particular, has been found to exhibit additive effects of this variety.

Concomitant use of Isosorbide Dinitrate with phosphodiesterase inhibitors in any form is contraindicated (see CONTRAINDICATIONS).

Concomitant use of Isosorbide Dinitrate with riociguat, a soluble guanylate cyclase stimulator, is contraindicated (see CONTRAINDICATIONS).

Carcinogenesis, Mutagenesis, Impairment of Fertility

No long-term studies in animals have been performed to evaluate the carcinogenic potential of isosorbide dinitrate. In a modified two-litter reproduction study, there was no remarkable gross pathology and no altered fertility or gestation among rats fed isosorbide dinitrate at 25 or 100 mg/kg/day.

Pregnancy

At oral doses 35 and 150 times the maximum recommended human daily dose, isosorbide dinitrate has been shown to cause a dose-related increase in embryotoxicity (increase in mummified pups) in rabbits. There are no adequate, well-controlled studies in pregnant women. Isosorbide dinitrate should be used during pregnancy only if the potential benefit justifies the potential risk to the fetus.

Nursing Mothers

It is not known whether isosorbide dinitrate is excreted in human milk. Because many drugs are excreted in human milk, caution should be exercised when isosorbide dinitrate is administered to a nursing woman.

Pediatric Use

Safety and effectiveness in pediatric patients have not been established.

Geriatric Use

Clinical studies of Isosorbide Dinitrate did not include sufficient numbers of subjects aged 65 and over to determine whether they respond differently from younger subjects. Other reported clinical experience has not identified differences in responses between the elderly and younger patients. In general, dose selection for an elderly patient should be cautious, usually starting at the low end of the dosing range, reflecting the greater frequency of decreased hepatic, renal, or cardiac function, and of concomitant disease or other drug therapy.

ADVERSE REACTIONS

Adverse reactions to isosorbide dinitrate are generally dose-related, and almost all of these reactions are the result of isosorbide dinitrate's activity as a vasodilator. Headache, which may be severe, is the most commonly reported side effect. Headache may be recurrent with each daily dose, especially at higher doses. Transient episodes of lightheadedness, occasionally related to blood pressure changes, may also occur. Hypotension occurs infrequently, but in some patients it may be severe enough to warrant discontinuation of therapy. Syncope, crescendo angina, and rebound hypertension have been reported but are uncommon.

Extremely rarely, ordinary doses of organic nitrates have caused methemoglobinemia in normal-seeming patients. Methemoglobinemia is so infrequent at these doses that further discussion of its diagnosis and treatment is deferred (see OVERDOSAGE).

Data are not available to allow estimation of the frequency of adverse reactions during treatment with Isosorbide Dinitrate tablets.

To report SUSPECTED ADVERSE REACTIONS, contact Oceanside Pharmaceuticals at 1-800-321-4576 or FDA at 1-800-FDA-1088 or www.fda.gov/medwatch.

OVERDOSAGE

Hemodynamic Effects

The ill effects of isosorbide dinitrate overdose are generally the results of isosorbide dinitrate's capacity to induce vasodilatation, venous pooling, reduced cardiac output, and hypotension. These hemodynamic changes may have protean manifestations, including increased intracranial pressure, with any or all of persistent throbbing headache, confusion, and moderate fever; vertigo; palpitations; visual disturbances; nausea and vomiting (possibly with colic and even bloody diarrhea); syncope (especially in the upright posture); air hunger and dyspnea, later followed by reduced ventilatory effort; diaphoresis, with the skin either flushed or cold and clammy; heart block and bradycardia; paralysis; coma; seizures; and death.

Laboratory determinations of serum levels of isosorbide dinitrate and its metabolites are not widely available, and such determinations have, in any event, no established role in the management of isosorbide dinitrate overdose.

There are no data suggesting what dose of isosorbide dinitrate is likely to be life-threatening in humans. In rats, the median acute lethal dose (LD50) was found to be 1100 mg/kg.

No data are available to suggest physiological maneuvers (e.g., maneuvers to change the pH of the urine) that might accelerate elimination of isosorbide dinitrate and its active metabolites. Similarly, it is not known which, if any, of these substances can usefully be removed from the body by hemodialysis.

No specific antagonist to the vasodilator effects of isosorbide dinitrate is known, and no intervention has been subject to controlled studies as a therapy for isosorbide dinitrate overdose. Because the hypotension associated with isosorbide dinitrate overdose is the result of venodilatation and arterial hypovolemia, prudent therapy in this situation should be directed toward increase in central fluid volume. Passive elevation of the patient's legs may be sufficient, but intravenous infusion of normal saline or similar fluid may also be necessary.

The use of epinephrine or other arterial vasoconstrictors in this setting is likely to do more harm than good.

In patients with renal disease or congestive heart failure, therapy resulting in central volume expansion is not without hazard. Treatment of isosorbide dinitrate overdose in these patients may be subtle and difficult, and invasive monitoring may be required.

Methemoglobinemia

Nitrate ions liberated during metabolism of isosorbide dinitrate can oxidize hemoglobin into methemoglobin. Even in patients totally without cytochrome b5 reductase activity, however, and even assuming that the nitrate moieties of isosorbide dinitrate are quantitatively applied to oxidation of hemoglobin, about 1 mg/kg of isosorbide dinitrate should be required before any of these patients manifests clinically significant (≥10%) methemoglobinemia. In patients with normal reductase function, significant production of methemoglobin should require even larger doses of isosorbide dinitrate. In one study in which 36 patients received 2 to 4 weeks of continuous nitroglycerin therapy at 3.1 to 4.4 mg/hr (equivalent, in total administered dose of nitrate ions, to 4.8 to 6.9 mg of bioavailable isosorbide dinitrate per hour), the average methemoglobin level measured was 0.2%; this was comparable to that observed in parallel patients who received placebo.

Notwithstanding these observations, there are case reports of significant methemoglobinemia in association with moderate overdoses of organic nitrates. None of the affected patients had been thought to be unusually susceptible.

Methemoglobin levels are available from most clinical laboratories. The diagnosis should be suspected in patients who exhibit signs of impaired oxygen delivery despite adequate cardiac output and adequate arterial pO2. Classically, methemoglobinemic blood is described as chocolate brown, without color change on exposure to air.

When methemoglobinemia is diagnosed, the treatment of choice is methylene blue, 1 to 2 mg/kg intravenously.

DOSAGE AND ADMINISTRATION

As noted under CLINICAL PHARMACOLOGY, multiple-dose studies with ISDN and other nitrates have shown that maintenance of continuous 24-hour plasma levels results in refractory tolerance. Every dosing regimen for Isosorbide Dinitrate tablets must provide a daily dose-free interval to minimize the development of this tolerance. With immediate-release ISDN, it appears that one daily dose-free interval must be at least 14 hours long.

As also noted under CLINICAL PHARMACOLOGY, the effects of the second and later doses have been smaller and shorter-lasting than the effects of the first.

Large controlled studies with other nitrates suggest that no dosing regimen with Isosorbide Dinitrate tablets should be expected to provide more than about 12 hours of continuous anti-anginal efficacy per day.

As with all titratable drugs, it is important to administer the minimum dose which produces the desired clinical effect. The usual starting dose of Isosorbide Dinitrate is 5 mg to 20 mg two or three times daily. For maintenance therapy, 10 mg to 40 mg two or three times daily is recommended. Some patients may require higher doses. A daily dose-free interval of at least 14 hours is advisable to minimize tolerance. The optimal interval will vary with the individual patient, dose and regimen.

HOW SUPPLIED

Isosorbide Dinitrate tablets are available as follows:

5 mg, round, pink tablets imprinted "BPI 152" on one side and deeply scored on reverse side:

NDC 68682-193-01, bottles of 100.

40 mg, round, light green tablets imprinted "BPI 192" on one side and deeply scored on reverse side:

NDC 68682-192-01, bottles of 100.

Store at 20° to 25°C (68° to 77°F); excursions permitted to 15° to 30°C (59° to 86°F) [see USP Controlled Room Temperature].

Protect from light.

Keep bottles tightly closed.

Dispense in a light-resistant, tight container.

Keep out of reach of children

Distributed by:
Oceanside Pharmaceuticals, a division of

Bausch Health US, LLC
Bridgewater, NJ 08807 USA

Manufactured by:
Bausch Health Companies Inc.
Steinbach, MB R5G 1Z7, Canada

© 2020 Bausch Health Companies Inc. or its affiliates

9704300 20002849

Rev. 03/2020

PRINCIPAL DISPLAY PANEL - 5 mg Label

NDC 68682-193-01

Rx only

Isosorbide Dinitrate Tablets
5 mg

100 Tablets

Oceanside Pharmaceuticals

PRINCIPAL DISPLAY PANEL - 40 mg Label

NDC 68682-192-01

Rx only

Isosorbide Dinitrate Tablets

40 mg

100 Tablets

Oceanside Pharmaceuticals

Contains FD&C Yellow No. 6 as a color additive.